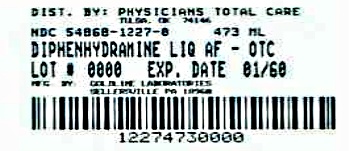 DRUG LABEL: Diphenhydramine Hydrochloride
NDC: 54868-1227 | Form: LIQUID
Manufacturer: Physicians Total Care, Inc.
Category: otc | Type: HUMAN OTC DRUG LABEL
Date: 20120605

ACTIVE INGREDIENTS: Diphenhydramine Hydrochloride 12.5 mg/5 mL
INACTIVE INGREDIENTS: citric acid monohydrate; D&C Red no. 33; FD&C Red  no. 40; glycerin; polysorbate 20; water; sodium benzoate; SACCHARIN SODIUM DIHYDRATE; sodium citrate; sorbitol

Hydramine Liquid 0182-6168-40

Drug Facts

Active ingredient (in each teaspoon (5 mL))

Diphenhydramine HCl USP 12.5 mg

Purpose

Antihistamine

Uses

temporarily relieves these symptoms due to hay fever or other upper respiratory allergies:

- runny nose
- sneezing
- itchy, watery eyes
- itching of the nose or throat

Warnings

Do not use

- to make a child sleepy
- with any other product containing diphenhydramine, even one used on skin

Ask a doctor before use if you have

- glaucoma
- trouble urinating due to an enlarged prostate gland
- a breathing problem such as emphysema or chronic bronchitis

Ask a doctor or pharmacist before use if you are taking sedatives or tranquilizers

When using this product

- marked drowsiness may occur
- avoid alcoholic drinks
- alcohol, sedatives, and tranquilizers may increase drowsiness
- be careful when driving a motor vehicle or operating machinery
- excitability may occur, especially in children

PREGNANCY OR BREAST FEEDING

If pregnant or breast-feeding, ask a health professional before use.

KEEP OUT OF REACH OF CHILDREN

Keep out of the reach of children. In case of overdose, get medical help or contact a Poison Control Center right away.

Directions

- take every 4 to 6 hours
- do not take more than 6 doses in 24 hours

adults and children 12 years and over | 2 to 4 teaspoons (25 mg to 50 mg)
children 6 to under 12 years | ask a doctor
children 4 to 5 years | do not use unless directed by a doctor
children under 4 years | do not use

Other information

- each teaspoon (5 mL) contains: sodium 5 mg
- store between 20°-25°C (68°-77°F). Protect from light.

Inactive ingredients

artificial cherry flavors, citric acid, D&C Red #33, FD&C Red #40, glycerin, polysorbate 20, purified water, sodium benzoate, sodium citrate, sodium saccharin, sorbitol solution

Questions?

call 1-888-838-2872, weekdays, 8 AM - 5 PM Eastern Time

PRINCIPAL DISPLAY PANEL

NDC 54868-1227-0

TAMPER-EVIDENT

Diphenhydramine HCl USP
12.5 mg per 5 mL)

ONE PINT (473 mL)

ANTIHISTAMINE

ALCOHOL-FREE
SUGAR-FREE
CHERRY-FLAVORED

TAMPER-EVIDENT: Do not use this product if
inner foil seal over the mouth of the bottle
is cut, torn, broken or missing.

NOT FOR HOUSEHOLDS
WITH YOUNG CHILDREN